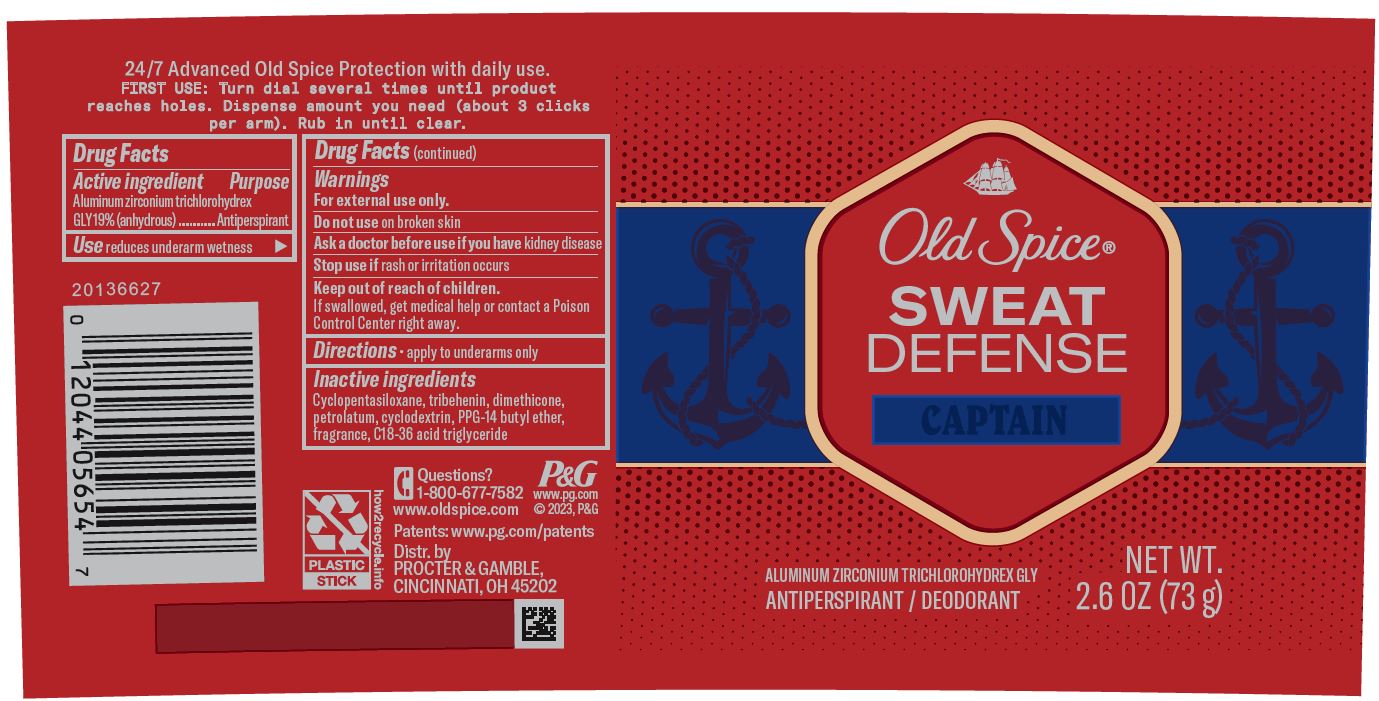 DRUG LABEL: Old Spice Sweat Defense Captain
NDC: 69423-740 | Form: CREAM
Manufacturer: The Procter & Gamble Manufacturing Company
Category: otc | Type: HUMAN OTC DRUG LABEL
Date: 20251231

ACTIVE INGREDIENTS: ALUMINUM ZIRCONIUM TRICHLOROHYDREX GLY 19 g/100 g
INACTIVE INGREDIENTS: DIMETHICONE; CYCLOMETHICONE 5; PETROLATUM; TRIBEHENIN; PPG-14 BUTYL ETHER; C18-36 ACID TRIGLYCERIDE; BETADEX

Old Spice® Sweat Defense Captain Soft Solid

Drug Facts

Active ingredient

Aluminum zirconium trichlorohydrex Gly 19% (anhydrous)

Purpose

Antiperspirant

Use

reduces underarm wetness

Warnings

For external use only.

Do not use on broken skin

Ask a doctor before use if you have kidney disease

Stop use if rash or irritation occurs

Keep out of reach of children.

If swallowed, get medical help or contact a Poison Control Center right away.

Directions

- apply to underarms only

Inactive ingredients

Cyclopentasiloxane, tribehenin, dimethicone, petrolatum, cyclodextrin, PPG-14 butyl ether, fragrance, C18-36 acid triglyceride

Questions?

1-800-677-7582

Dist. by PROCTER & GAMBLE,
CINCINNATI, OH 45202.

PRINCIPAL DISPLAY PANEL - 73 g Cylinder Label

Old Spice®

SWEAT

DEFENSE

CAPTAIN

ALUMINUM ZIRCONIUM TRICHLOROHYDREX GLY

ANTIPERSPIRANT/DEODORANT

NET WT.

2.6 OZ (73 g)